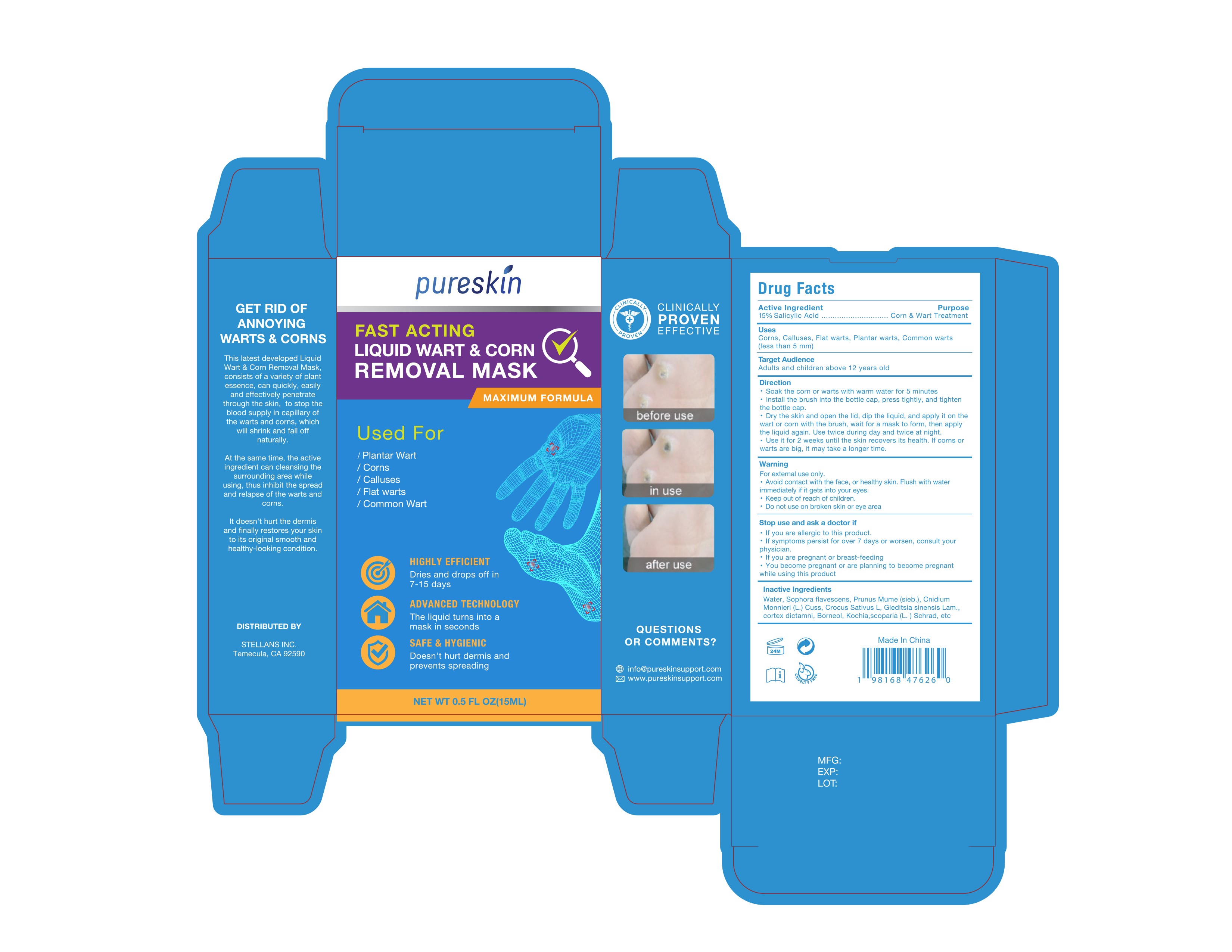 DRUG LABEL: Pureskin Liquid Wart  Corn Removal Mask
NDC: 84746-007 | Form: LIQUID
Manufacturer: Shandong Yuyaotang Pharmaceutical Co., Ltd
Category: otc | Type: HUMAN OTC DRUG LABEL
Date: 20250325

ACTIVE INGREDIENTS: SALICYLIC ACID 15 g/100 mL
INACTIVE INGREDIENTS: DICTAMNUS DASYCARPUS ROOT BARK; WATER; CNIDIUM MONNIERI WHOLE; SOPHORA FLAVESCENS WHOLE; CROCUS SATIVUS WHOLE; GLEDITSIA SINENSIS WHOLE; BORNEOL; PRUNUS MUME WHOLE; BASSIA SCOPARIA WHOLE

84746-007

Active Ingredient

15% Salicylic Acid

Purpose

Corn & Wart Treatment

Use

Corns, Calluses, Flat warts, Plantar warts, Common warts (less than 5 mm)

Warnings

For external use only.
Avoid contact with the face, or healthy skin. Flush with water immediately if it gets into your eyes.

Do not use on broken skin or eye area

When Using

Avoid contact with the face, or healthy skin. Flush with water immediately if it gets into your eyes.

Stop Use

If you are allergic to this product.
If symptoms persist for over 7 days or worsen

Ask Doctor

• If you are allergic to this product.
• If symptoms persist for over 7 days or worsen, consult your physician.
• If you are pregnant or breast-feeding
• You become pregnant or are planning to become pregnant while using this product

Keep Oot Of Reach Of Children

Keep out of reach of children

Directions

• Soak the corn or warts with warm water for 5 minutes
• Instail the brush into the bottle cap, press tightly, and tighten the bottle cap.
• Dry the skin and open the lid, dip the liquid, and apply it on the wart or corn with the brush, wait for a mask to form, then apply the liquid again. Use twice during day and twice at night.
• Use it for 2 weeks until the skin recovers its health. If corns or warts are big, it may take a longer time.

Inactive ingredients

Water, Sophora flavescens, Prunus Mume (sieb.), Cnidium Monnieri (L.) Cuss, Crocus Sativus L, Gleditsia sinensis Lam., cortex dictamni, Borneol, Kochia scoparia (L.) Schrad

Questions

info@pureskinsupport.com
www.pureskinsupport.com